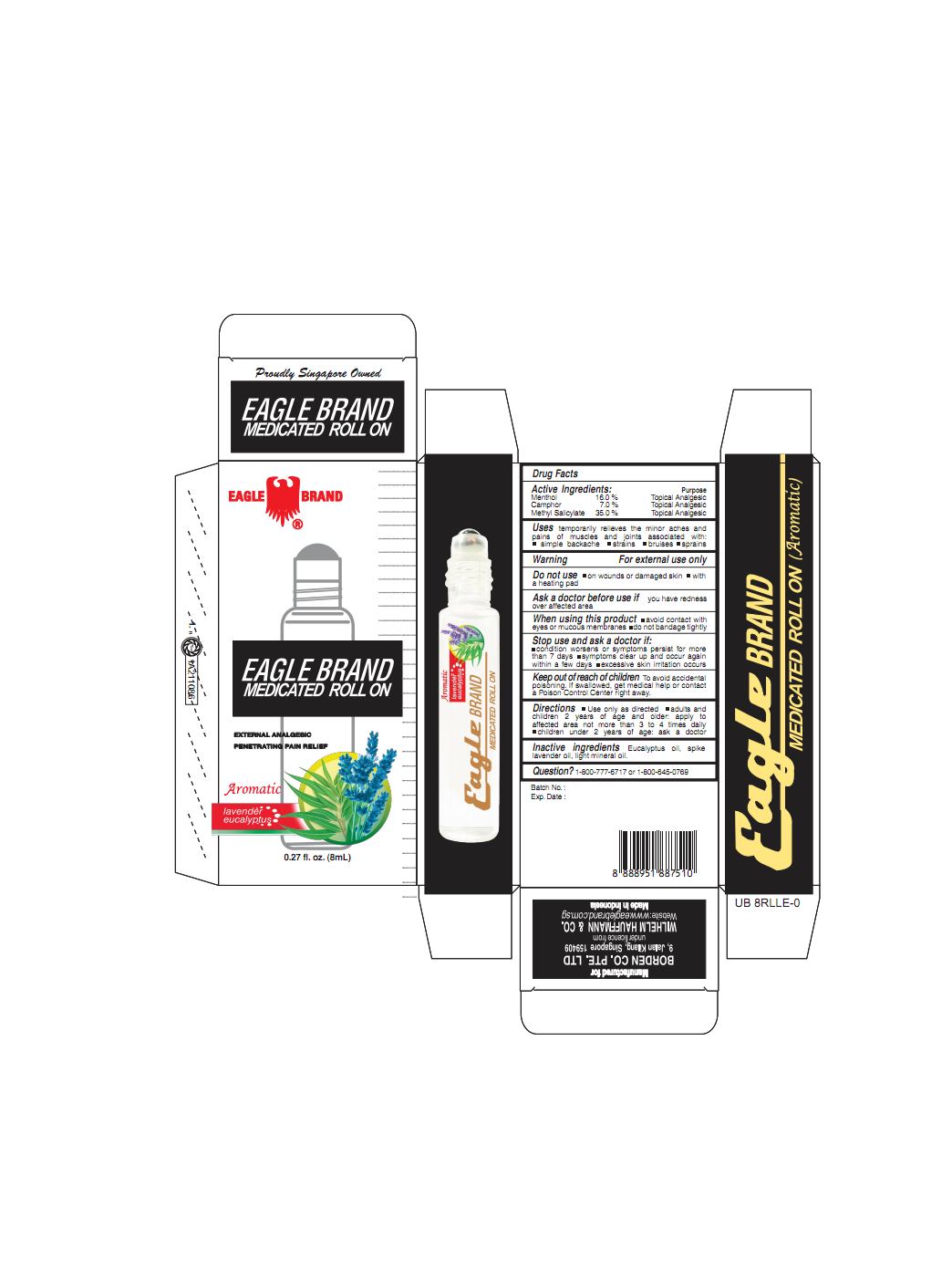 DRUG LABEL: Eagle
NDC: 60954-007 | Form: OIL
Manufacturer: Eagle Indo Pharma, PT
Category: otc | Type: HUMAN OTC DRUG LABEL
Date: 20241002

ACTIVE INGREDIENTS: CAMPHOR (SYNTHETIC) 7 g/100 mL; MENTHOL 16 g/100 mL; METHYL SALICYLATE 35 g/100 mL
INACTIVE INGREDIENTS: EUCALYPTUS OIL; LIGHT MINERAL OIL; SPIKE LAVENDER OIL

Eagle Medicated Oil Aromatic

Active Ingredients

Camphor 7%

Menthol 16%
Methyl Salicylate 35%

Purpose

Topical Analgesic

Topical Analgesic

Topical Analgesic

Uses

temporarily relieves the minor aches and pains of muscles and joint associated with ■ simple backache ■ strains

■ bruises ■ sprains

Warning

For external use only

Do not use

■ on wounds or damaged skin ■ with a heating pad

Ask a doctor before use if

you have redness over affected area

When using this product

■ avoid contact with eyes or mucous membranes ■ do not bandage tightly

Stop use and ask a doctor if

■condition worsens, or if symptoms persist for more than 7 days ■symptoms clear up and occur again within a few days ■ excessive skin irritation occurs

Keep out of reach of children

Keep out of reach of childrenTo avoid accidental poisoning. If swallowed, get medical help or contact a Poison Control Center right away

Directions

■ Use only as directed ■ adults and children 2 years of age and older: apply to affected area not more than 3 to 4 times daily. ■children under 2 years of age: ask a doctor

Inactive ingredients

eucalyptus oil, spike lavender oil, light mineral oil

Question?

1-800-777-6717 or 1-800-645-0769